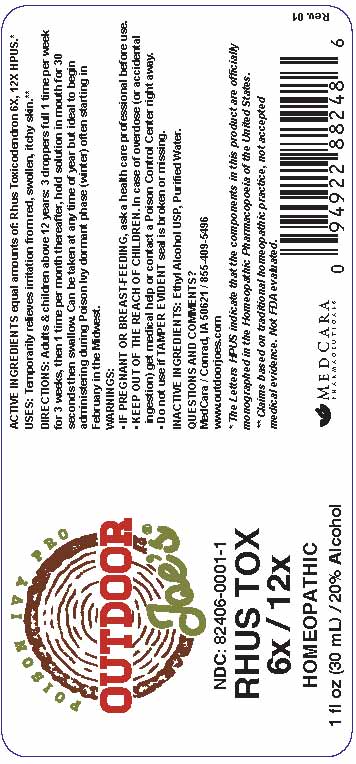 DRUG LABEL: Rhus Tox 6x/12x
NDC: 82406-0001 | Form: LIQUID
Manufacturer: MedCara Pharmaceuticals, LLC
Category: homeopathic | Type: HUMAN OTC DRUG LABEL
Date: 20220303

ACTIVE INGREDIENTS: TOXICODENDRON PUBESCENS LEAF 12 [hp_X]/1 mL
INACTIVE INGREDIENTS: ALCOHOL; WATER

RHUS TOX 6x/12x

ACTIVE INGREDIENT

ACTIVE INGREDIENTS equal amounts of: Rhus Toxicodendron 6X, 12X HPUS*

INDICATIONS AND USAGE

USES: Temporarily relieves irritation from red, swollen, itchy skin.**

PURPOSE

USES: Temporarily relieves irritation from red, swollen, itchy skin.**

DOSAGE AND ADMINISTRATION

DIRECTIONS: Adults and children above 12 years: 3 droppers full 1 time per week for 3 weeks, then 1 time per month thereafter, hold solution in mouth for 30 seconds then swallow. Can be taken at any time of year but ideal to begin administering during Poison Ivy dormant phase (winter) often starting in February in the Midwest.

KEEP OUT OF REACH OF CHILDREN

KEEP OUT OF THE REACH OF CHILDREN. In case of overdose (or accidental ingestion) get medical help or contact a Poison Control Center right away.

WARNINGS:

- Consult a physician for use in children under 12 years of age.
- IF PREGNANT OR BREAST-FEEDING, ask a health care professional before use.
- KEEP OUT OF THE REACH OF CHILDREN. In case of overdose (or accidental ingestion) get medical help or contact a Poison Control Center right away.
- Do not use if TAMPER EVIDENT seal is broken or missing.

INACTIVE INGREDIENTS: Ethyl Alcohol USP, Purified Water.

QUESTIONS & COMMENTS?

MedCara / Conrad, IA 50621 / 855-409-5496

www.outdoorjoes.com

REFERENCES

*The letters "HPUS" indicate the components in the products are officially monographed in the Homeopathic Pharmacopeia of the United States.

**Claims based on traditional homeopathic practice, not accepted medical evidence. Not FDA evaluated.

PACKAGE LABEL

NDC: 82406-0001-1

RHUS TOX 6X / 12X

Homeopathic

1 fl oz (30 mL) / 20% Alcohol